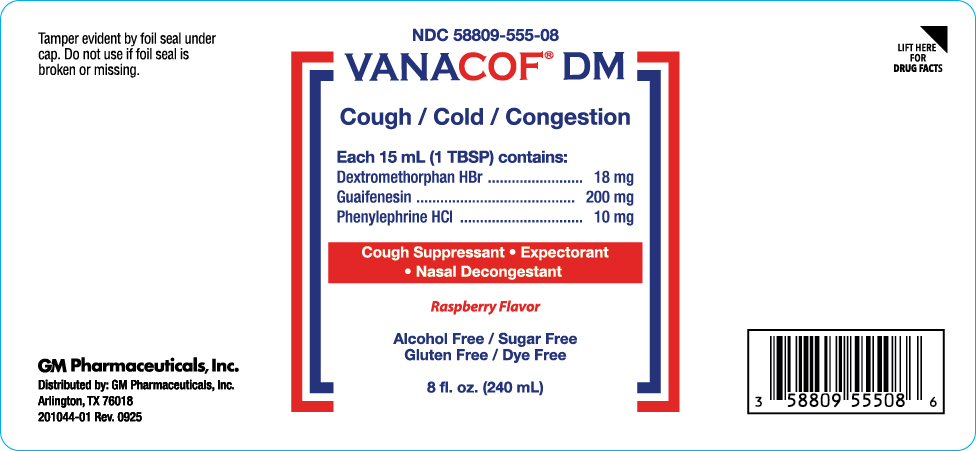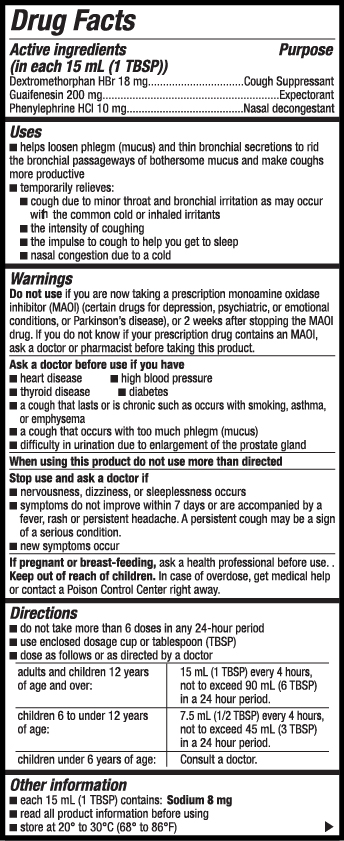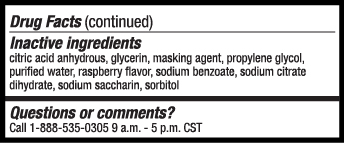 DRUG LABEL: VANACOF DM
NDC: 58809-555 | Form: LIQUID
Manufacturer: GM Pharmaceuticals, INC
Category: otc | Type: HUMAN OTC DRUG LABEL
Date: 20251103

ACTIVE INGREDIENTS: DEXTROMETHORPHAN HYDROBROMIDE 18 mg/15 mL; GUAIFENESIN 200 mg/15 mL; PHENYLEPHRINE HYDROCHLORIDE 10 mg/15 mL
INACTIVE INGREDIENTS: ANHYDROUS CITRIC ACID; GLYCERIN; PROPYLENE GLYCOL; WATER; TRISODIUM CITRATE DIHYDRATE; SACCHARIN SODIUM; SORBITOL; SODIUM BENZOATE

Vanacof DM

Vanacof DM

NDC 58809-555-08

8 fl. Oz. (240 mL)

Active ingredients (in each 15 mL (1 TBSP))

Dextromethorphan HBr 18 mg

Guaifenesin 200 mg

Phenylephrine HCl 10 mg

Purpose

Cough Suppressant

Expectorant

Nasal Decongestant

Uses

- helps loosen phlegm (mucus) and thin bronchial secretions to rid the bronchial passageways of bothersome mucus and make coughs more productive
- temporarily relieves:
  - cough due to minor throat and bronchial irritation as may occur with the common cold or inhaled irritants
  - the intensity of coughing
  - the impulse to cough to help you get to sleep
  - nasal congestion due to a cold

Warnings

Do not use

if you are now taking a prescription monoamine oxidase inhibitor (MAOI) (certain drugs for depression, psychiatric, or emotional conditions, or Parkinson's disease), or for 2 weeks after stopping the MAOI drug. If you do not know if your prescription drug contains an MAOI, ask a doctor or pharmacist before taking this product.

Ask a doctor before use if you have

- heart disease
- high blood pressure
- thyroid disease
- diabetes
- a cough that lasts or is chronic such as occurs with smoking, asthma, or emphysema
- a cough that occurs with too much phlegm (mucus)
- difficulty in urination due to enlargement of the prostate gland

When using this product

do not use more than directed

Stop use and ask a doctor if:

- nervousness, dizziness or sleeplessness occurs
- symptoms do not improve within 7 days or are accompanied by a fever, rash or persistent headache. A persistant cough may be a sign of a serious condition.
- new symptoms occur

If pregnant or breast-feeding,

ask a health professional before use.

Keep out of reach of children.

In case of overdose, get medical help or contact a Poison Control Center right away.

Directions

- do not take more than 6 doses in any 24-hour period
- use enclosed dosage cup or tablespoon (TBSP)
- dose as follows or as directed by a doctor

Adults and children 12 years of age and over: | 15 mL (1 TBSP) every 4 hours, not to exceed 90 mL (6 TBSP) in a 24 hour period.
Children 6 to under 12 years of age: | 7.5 mL (1/2 TBSP) every 4 hours, not to exceed 45 mL (3 TBSP) in a 24 hour period.
Children under 6 years of age: | Consult a doctor.

Other information

- Each 15 mL (TBSP) contains: Sodium 8 mg.
- read all product information before using
- store at 20-30°C (68-86°F)

Inactive ingredients

citric acid anhydrous, glycerin, masking agent, propylene glycol, purified water, raspberry flavor, sodium benzoate, sodium citrate dihydrate, sodium saccharin, sorbitol

Questions or Comments?

Call 1-888-535-0305 9 a.m. - 5 p.m. CST.

Distributed by:

GM Pharmaceuticals, Inc.

Arlington, TX 76018

KEEP LEAFLET AFTER OPENING

Rev. 09/25

PRINCIPAL DISPLAY PANEL

NDC 58809-555-08
VANACOF DM
Cough
Cold/Congestion
Raspberry Flavor
8 fl. oz. (240 mL)